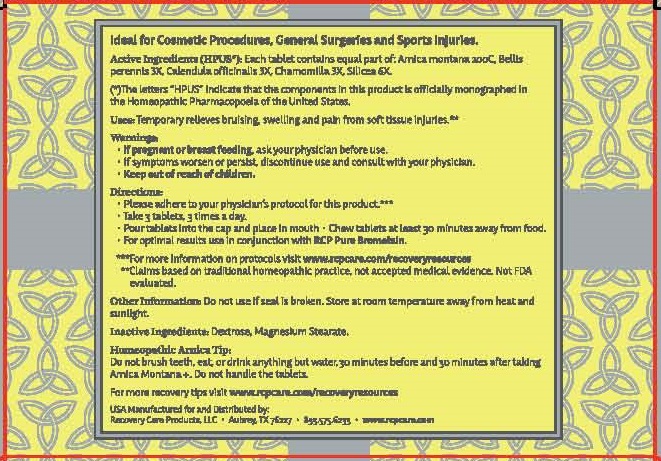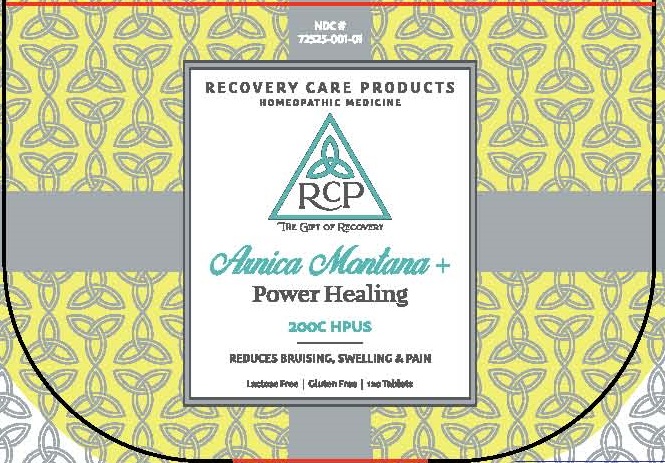 DRUG LABEL: Arnica Montana  Power Healing
NDC: 72525-001 | Form: TABLET, CHEWABLE
Manufacturer: Recovery Care Products LLC
Category: homeopathic | Type: HUMAN OTC DRUG LABEL
Date: 20220117

ACTIVE INGREDIENTS: ARNICA MONTANA 200 [hp_C]/1 1; BELLIS PERENNIS 3 [hp_X]/1 1; CALENDULA OFFICINALIS FLOWERING TOP 3 [hp_X]/1 1; MATRICARIA CHAMOMILLA 3 [hp_X]/1 1; SILICON DIOXIDE 6 [hp_X]/1 1
INACTIVE INGREDIENTS: DEXTROSE; MAGNESIUM STEARATE

RECOVERY CARE PRODUCTS Arnica Montana + Healing Power (72525-001)

Active Ingredients (HPUS*):

Each tablet contains equal part of: Arnica montana 200C, Bellis perennis 3X, Calendula officinalis 3X, Chamomilla 3X, Silicea 6X.(*)The letters "HPUS" indicate that the components in this prodcut is officially monographed inthe Homeopathic Pharmacopoeia of the United States.**Claims based on traditional homeopathic practice, not accepted medical evidence. Not FDA evaluated.

PURPOSE

REDUCES BRUISING, SWELLING & PAIN

Uses:

Temporary relieves bruising, swelling and pain from soft tissue injuries.**

Warnings:

• If pregnant or breast feeding, ask your physician before use.
• If symptoms worsen or persist, discontinue use and consult with your physician.

• Keep out of reach of children.

Directions:

• Please adhere to your physician’s protocol for this product.***
• Take 3 tablets, 3 times a day
• Pour tablets into the cap and place in mouth • Chew tablets at least 30 minutes away from food.
• For optimal results use in conjunction with RCP Pure Bromelain

Other Information:

Do not use if seal is broken. Store at room temperature away from heat and
sunlight

Inactive Ingredients:

Dextrose, Magnesium Stearate.

QUESTIONS

***For more information on protocols visit www.rcpcare.com/recoveryresources

USA Manufactured for and Distributed by:

Recovery Care Products, LLC • Aubrey, TX 76227 • 833.575.6233 • www.rcpcare.com